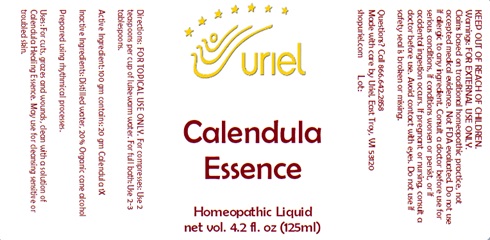 DRUG LABEL: Calendula Essence
NDC: 48951-3256 | Form: LIQUID
Manufacturer: Uriel Pharmacy Inc.
Category: homeopathic | Type: HUMAN OTC DRUG LABEL
Date: 20241202

ACTIVE INGREDIENTS: CALENDULA OFFICINALIS FLOWERING TOP 1 [hp_X]/1 mL
INACTIVE INGREDIENTS: WATER; ALCOHOL

Calendula Essence

INDICATIONS AND USAGE

Directions: FOR TOPICAL USE ONLY.

DOSAGE AND ADMINISTRATION

For compresses: Use 2 teaspoons per cup of lukewarm water. For full bath: Use 2-3 tablespoons.

Active Ingredient: 100 gm contains: 20 gm Calendula 1X

Inactive Ingredients: Distilled water, 20% Organic cane alcohol

PURPOSE

Uses: For cuts, grazes and wounds, clean with a solution of Calendula Healing Essence. May use for cleansing sensitive or troubled skin.

KEEP OUT OF REACH OF CHILDREN.

Warnings: FOR EXTERNAL USE ONLY.
Claims based on traditional homeopathic practice, not accepted medical evidence. Not FDA evaluated. Do not use if allergic to any ingredient. Consult a doctor before use for serious conditions, if conditions worsen or persist, or if accidental ingestion occurs. If pregnant or nursing, consult a doctor before use. Avoid contact with eyes. Do not use if safety seal is broken or missing.

QUESTIONS

Questions? Call 866.642.2858 Made with care by Uriel, East Troy, WI 53120 shopuriel.com Lot: